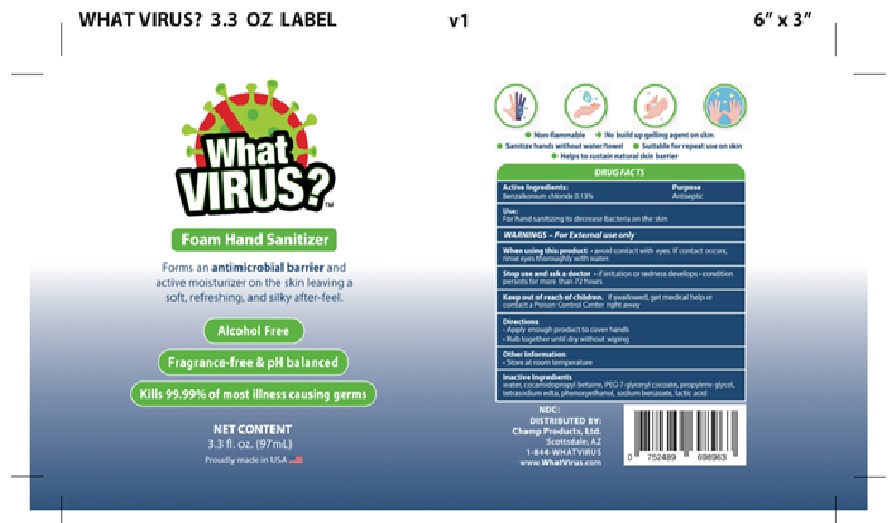 DRUG LABEL: WHAT VIRUS
NDC: 78658-002 | Form: LIQUID
Manufacturer: Champ Products, Ltd
Category: otc | Type: HUMAN OTC DRUG LABEL
Date: 20210209

ACTIVE INGREDIENTS: BENZALKONIUM CHLORIDE 0.13 g/100 mL
INACTIVE INGREDIENTS: WATER; COCAMIDOPROPYL BETAINE; PEG-7 GLYCERYL COCOATE; PROPYLENE GLYCOL; EDETATE SODIUM; PHENOXYETHANOL; SODIUM BENZOATE; LACTIC ACID

Active Ingredient

Benzalkonium Chloride 0.13%

Purpose

Antiseptic

Uses

For hand sanitizing to decrease bacteria on the skin
Rub together until dry without wiping

Directions

Apply enough product to cover hands.
Rub together without wiping.

Warnings

For external use only.

When using this product: avoid contact with eyes. If contact occurs, rinse eyes thoroughly with water.

Stop use and ask a doctor: if irritation or redness develops - condition persists for more than 72 hours.

Keep out of reach of children

If swallowed, get medical help or contact a Poison Control Center right away.

Inactive ingredients

WATER, COCAMIDOPROPYL BETAINE, PEG-7 GLYCERYL COCOATE, PROPYLENE GLYCOL, TETRASODIUM EDTA, PHENOXYETHANOL, SODIUM BENZOATE, LACTIC ACID

Other information

Store at room temperature.